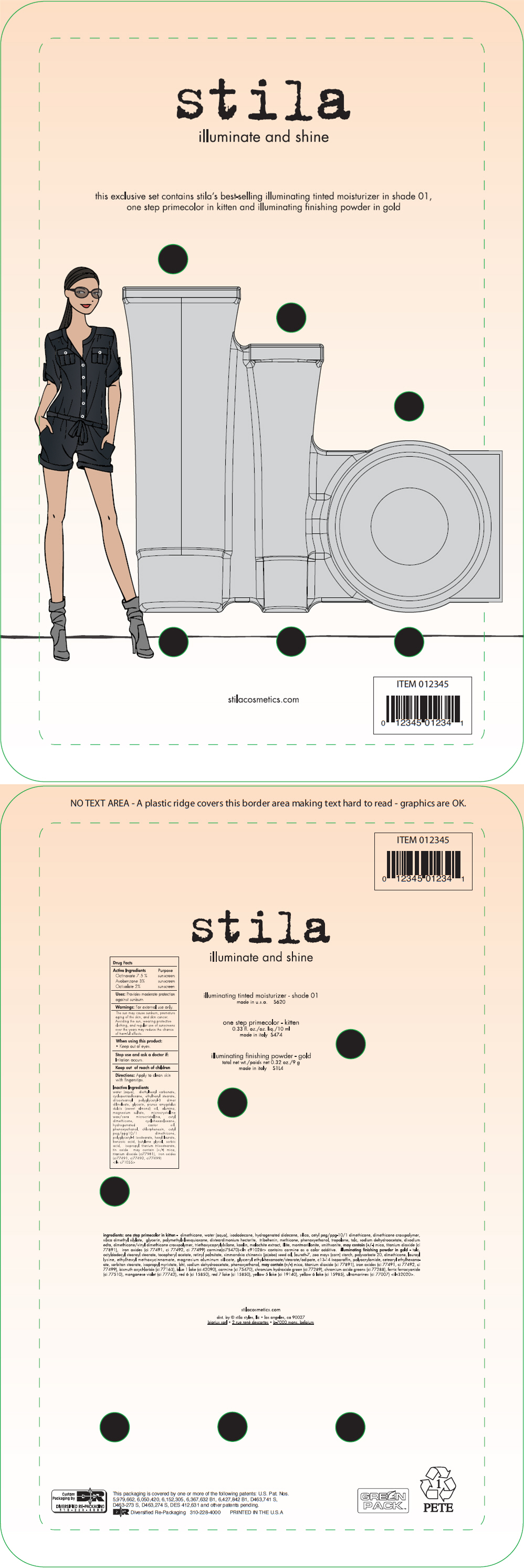 DRUG LABEL: stila illuminate and shine
NDC: 76049-620 | Form: KIT | Route: TOPICAL
Manufacturer: Stila Styles, LLC
Category: otc | Type: HUMAN OTC DRUG LABEL
Date: 20131125

ACTIVE INGREDIENTS: Octinoxate 75 mg/1 mL; Avobenzone 30 mg/1 mL; Octisalate 20 mg/1 mL
INACTIVE INGREDIENTS: water; diethylhexyl carbonate; cyclomethicone 5; ethylhexyl stearate; diisostearoyl polyglyceryl-3 dimer dilinoleate; glycerin; almond oil; aluminum oxide; magnesium sulfate; microcrystalline wax; cyclomethicone 6; hydrogenated castor oil; phenoxyethanol; chlorphenesin; polyglyceryl-4 isostearate; hexyl laurate; benzoic acid; butylene glycol; sorbic acid; isopropyl titanium triisostearate; stannic oxide; mica; titanium dioxide; ferric oxide red; ferric oxide yellow; ferrosoferric oxide

stila illuminate and shine

illuminating tinted moisturizer - shade 01

Drug Facts

ACTIVE INGREDIENT

Active Ingredients | Purpose
Octinoxate 7.5 % | sunscreen
Avobenzone 3% | sunscreen
Octisalate 2% | sunscreen

Uses

Provides moderate protection against sunburn

Warnings

For external use only.

The sun may cause sunburn, premature aging of the skin, and skin cancer. Avoiding the sun, wearing protective clothing, and regular use of sunscreens over the years may reduce the chance of harmful effects.

When using this product

- Keep out of eyes.

Stop use and ask a doctor if

Irritation occurs.

Keep out of reach of children

Directions

Apply to clean skin with fingerstips.

Inactive Ingredients

water (aqua), diethylhexyl carbonate, cyclopentasiloxane, ethylhexyl stearate, diisostearoyl polyglyceryl-3 dimer dilinoleate, glycerin, prunus amygdalus dulcis (sweet almond) oil, alumina, magnesium sulfate, microcrystalline wax/cera microcristallina, cetyl dimethicone, cyclohexasiloxane, hydrogenated castor oil, phenoxyethanol, chlorphenesin, cetyl peg/ppg10/1 dimethicone, polyglyceryl-4 isostearate, hexyl laurate, benzoic acid, butylene glycol, sorbic acid, isopropyl titanium triisostearate, tin oxide may contain (+/-) mica, titanium dioxide (ci77981), iron oxides (ci77491, ci77492, ci77499) <iln c71055>

dist. by © stila styles, llc • los angeles, ca 90027

PRINCIPAL DISPLAY PANEL - Kit Label

stila
illuminate and shine

this exclusive set contains stila's best-selling illuminating tinted moisturizer in shade 01,
one step primecolor in kitten and illuminating finishing powder in gold

stilacosmetics.com